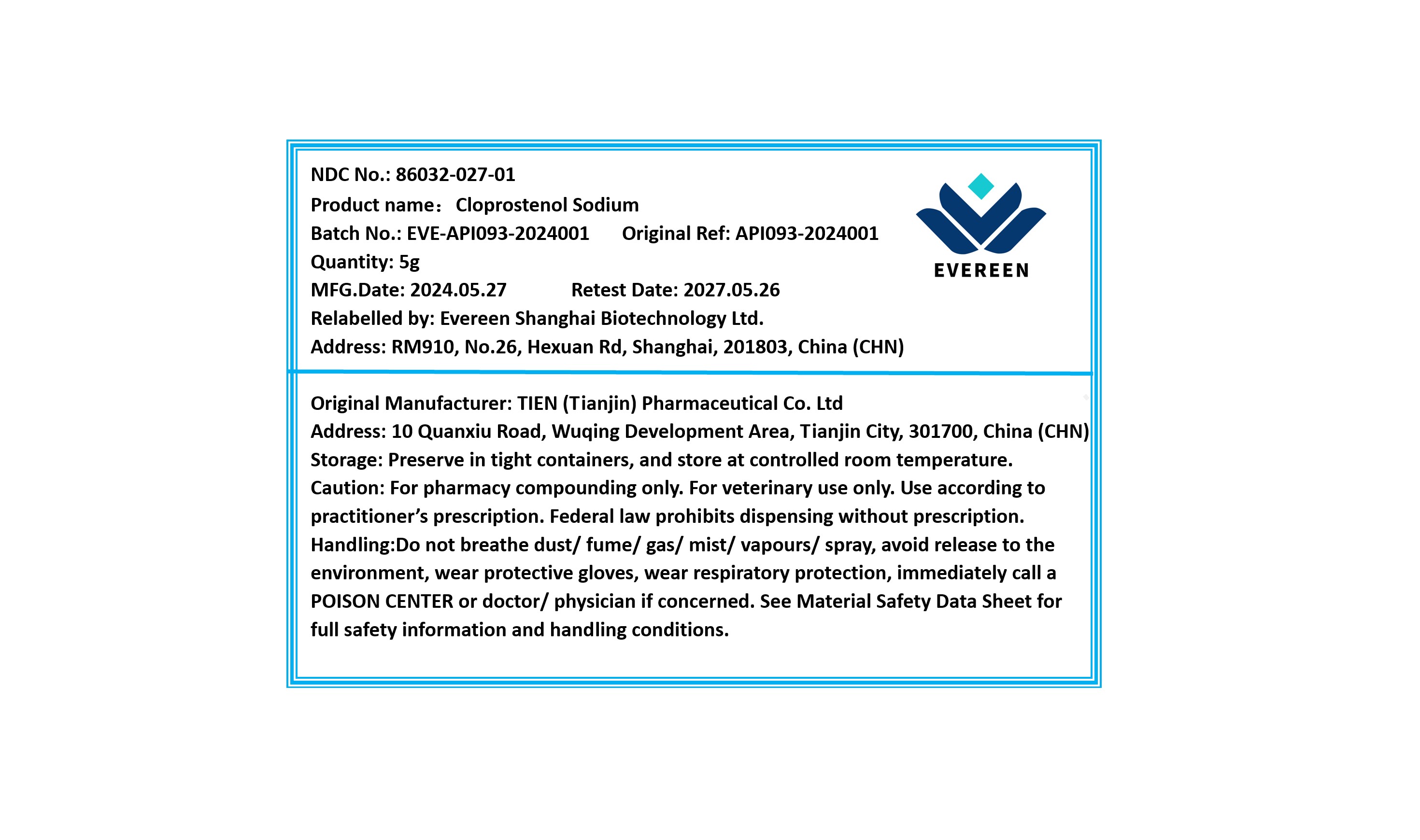 DRUG LABEL: Cloprostenol Sodium
NDC: 86032-027 | Form: POWDER
Manufacturer: Evereen Shanghai Biotechnology Ltd.
Category: other | Type: BULK INGREDIENT - ANIMAL DRUG
Date: 20240820

ACTIVE INGREDIENTS: CLOPROSTENOL SODIUM 1 g/1 g

Cloprostenol Sodium